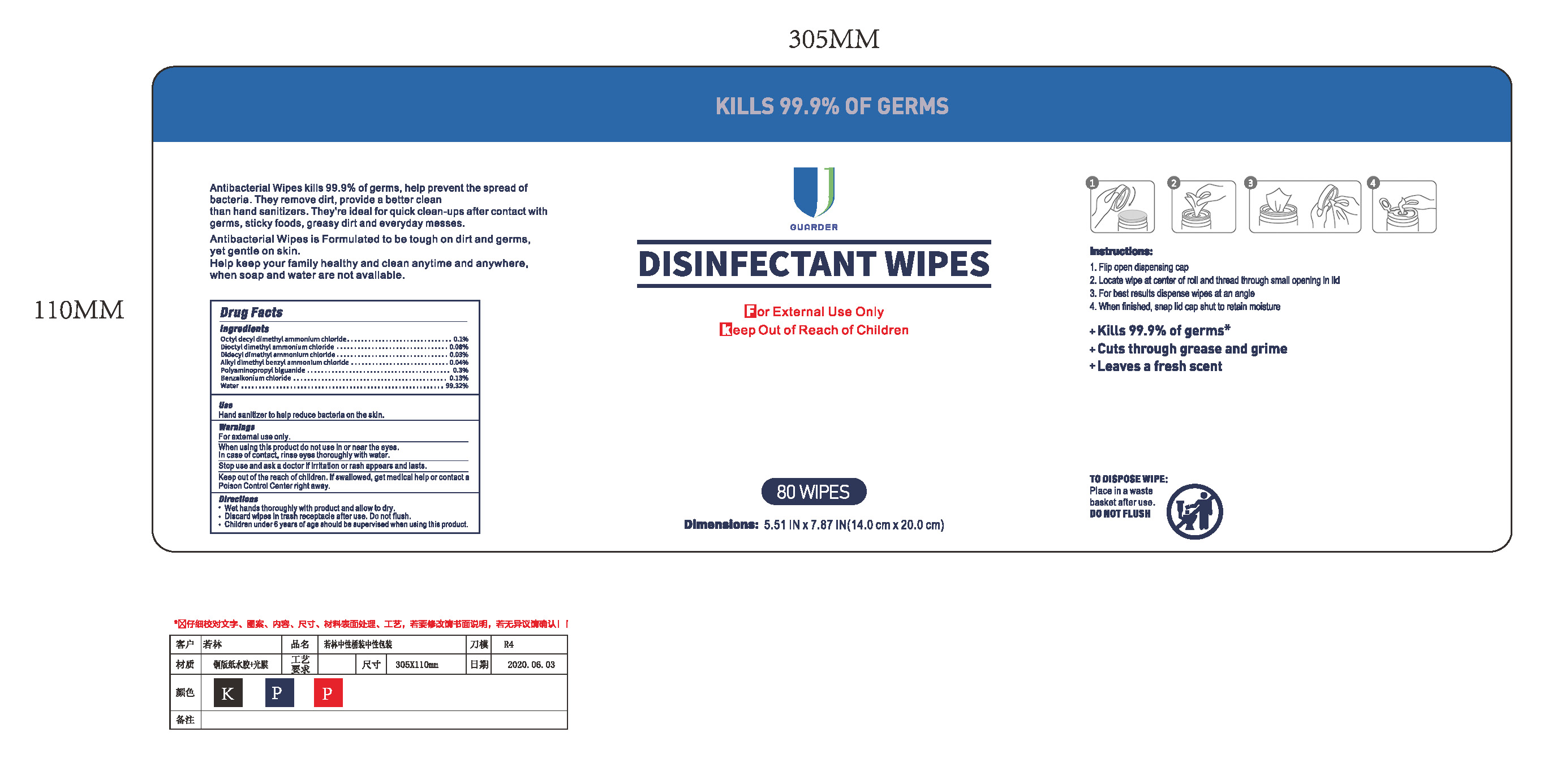 DRUG LABEL: Disinfectant wipes
NDC: 79795-002 | Form: CLOTH
Manufacturer: NanTong Guarder Medical Technology Co.,Ltd.
Category: otc | Type: HUMAN OTC DRUG LABEL
Date: 20200728

ACTIVE INGREDIENTS: DIDECYLDIMONIUM CHLORIDE 0.03 g/100 1; BENZALKONIUM CHLORIDE 0.13 g/100 1; POLYAMINOPROPYL BIGUANIDE 0.3 g/100 1; QUATERNIUM-24 0.1 g/100 1
INACTIVE INGREDIENTS: DIOCTYLDIMONIUM CHLORIDE 0.08 g/100 1; WATER

Disinfectant wipes

Active Ingredient(s)

Octyl decyl dimethyl ammonium chloride 0.1%

Dioctyl dimethyl ammonium chloride 0.08%

Didecyl dimethyl ammonium chloride 0.03%

Alkyl dimethyl benzyl ammonium chloride 0.04%

Polyaminopropyl biguanide 0.3%

Benzalkonium chloride 0.13%

Purpose: Antiseptic

Purpose

Antiseptic

Use

Hand Sanitizer to help reduce bacteria on the skin.

Warnings

For external use only. Flammable.
When using this product keep out of eyes, ears, and mouth. In case of contact with eyes, rinse eyes thoroughly with water.
Stop use and ask a doctor if irritation or rash appears and lasts.
Keep out of the reach of children. If swallowed, get medcial help or contact a poison control center right away.

Do not use

Wet hands thoroughly with product and allow to dry.
Dicard wipes in trash receptacle after use. Do not flush.
Children under 6 years of age should be supervised when using this product.

When using this product keep out of eyes, ears, and mouth. In case of contact with eyes, rinse eyes thoroughly with water.
Stop use and ask a doctor if irritation or rash occurs. These may be signs of a serious condition.
Keep out of reach of children. If swallowed, get medical help or contact a Poison Control Center right away.

Stop use and ask a doctor if irritation or rash occurs. These may be signs of a serious condition.

Keep out of reach of children. If swallowed, get medical help or contact a Poison Control Center right away.

Directions

Wet hands thoroughly with product and allow to dry.
Dicard wipes in trash receptacle after use. Do not flush.
Children under 6 years of age should be supervised when using this product.

Other information

- Store between 15-30C (59-86F)
- Avoid freezing and excessive heat above 40C (104F)

Inactive ingredients

Water

Package Label - Principal Display Panel

80wipes in 1box NDC: 79795-002-09